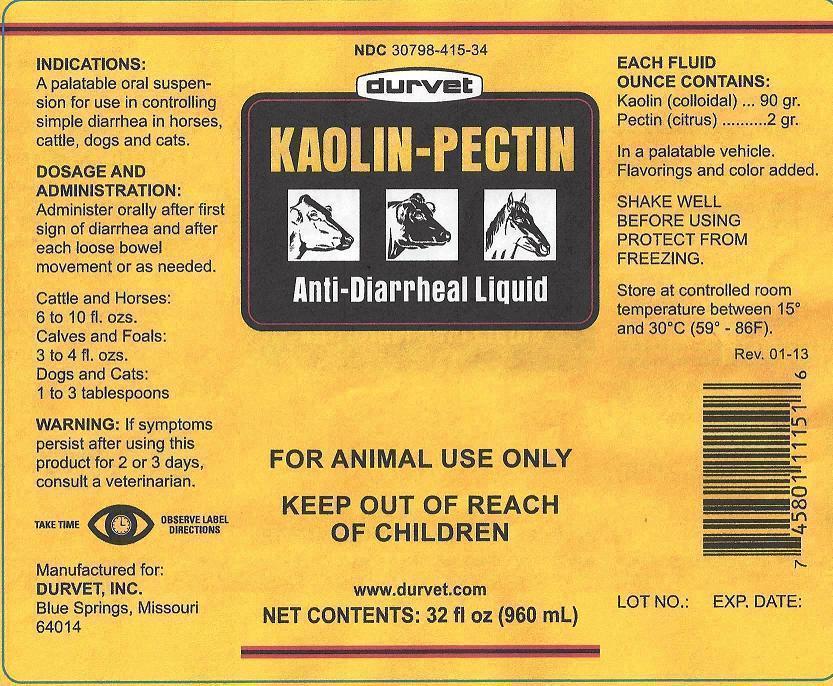 DRUG LABEL: Kaolin Pectin
NDC: 30798-415 | Form: SUSPENSION
Manufacturer: Durvet, Inc.
Category: animal | Type: OTC ANIMAL DRUG LABEL
Date: 20131216

ACTIVE INGREDIENTS: KAOLIN 196 mg/1 mL; PECTIN, CITRUS 4.5 mg/1 mL
INACTIVE INGREDIENTS: GUAR GUM; METHYLPARABEN; POTASSIUM SORBATE; SACCHARIN SODIUM; PROPYLPARABEN; FD&C RED NO. 40; WATER

Durvet Kaolin-Pectin Anti-Diarrheal Liquid

INDICATIONS

A palatable oral suspension for use in controlling simple diarrhea in horses, cattle, dogs and cats.

DOSAGE AND ADMINISTRATION

Administer orally after first sign of diarrhea and after each loose bowel movement or as needed.

Cattle and Horses:
6 to 10 fl. ozs.

Calves and Foals:
3 to 4 fl. ozs.

Dogs and Cats:
1 to 3 tablespoons

WARNING

If symptoms persist after using this product for 2 or 3 days, consult a veterinarian.

TAKE TIME OBSERVE LABEL DIRECTIONS

EACH FLUID OUNCE CONTAINS:

Kaolin (colloidal) ... 90 gr.

Pectin (citrus) ........... 2 gr.

In a palatable vehicle.

Flavorings and color added.

SHAKE WELL BEFORE USING

PROTECT FROM FREEZING

STORAGE

Store at controlled room temperature between 15º and 30ºC (59º - 86F).

Manufactured for:

DURVET, INC.
Blue Springs, Missouri
64014

Package/Label Principal Display Panel

durvet

KAOLIN-PECTIN
Anti-Diarrheal Liquid

FOR ANIMAL USE ONLY

KEEP OUT OF REACH OF CHILDREN

www.durvet.com

NET CONTENTS: 32 fl oz (960 mL)

Manufactured for:

DURVET, INC.
Blue Springs, Missouri
64014

Bottle Label